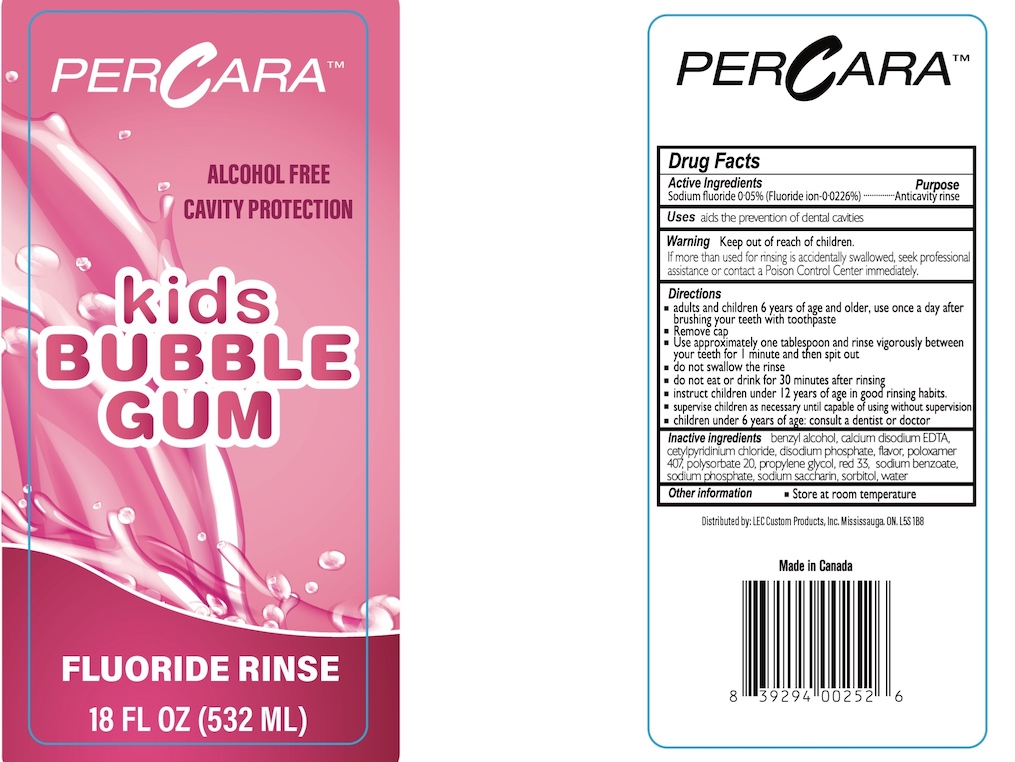 DRUG LABEL: PerCara Kids Bubble Gum
NDC: 67933-0016 | Form: RINSE
Manufacturer: LEC Custom Products, Inc.
Category: otc | Type: HUMAN OTC DRUG LABEL
Date: 20240101

ACTIVE INGREDIENTS: SODIUM FLUORIDE 0.05 g/100 mL
INACTIVE INGREDIENTS: BENZYL ALCOHOL; EDETATE CALCIUM DISODIUM ANHYDROUS; CETYLPYRIDINIUM CHLORIDE; POLOXAMER 407; POLYSORBATE 80; PROPYLENE GLYCOL; D&C RED NO. 33; SODIUM BENZOATE; SODIUM PHOSPHATE; SODIUM PHOSPHATE DIBASIC DIHYDRATE; SACCHARIN SODIUM; SORBITOL; WATER

PerCara Bubblegum Fluoride Rinse

Drug Facts

Active Ingredients

Sodium fluoride 0.05% (Fluoride ion-0.0226%)

Purpose

Anticavity rinse

Uses

aids the prevention of dental cavities

Warning

Keep out of reach of children. If more than used for rinsing is accidentally swallowed, get medical help or contact a Poison Control Center immediately.

Directions

- adults and children 6 years of age and older, use once a day after brushing your teeth with a toothpaste
- Remove cap
- Use approximately one tablespoon and rinse vigorously between your teeth for 1 minute and then spit out
- do not swallow the rinse
- do not eat or drink for 30 minutes after rinsing
- instruct children under 12 years of age in good rinsing habits
- supervise children as necessary until capable of using without supervision
- children under 6 years of age: consult a dentist or doctor

INACTIVE INGREDIENT

Inactive ingredients benzyl alcohol, calcium disodium EDTA, cetylpyridinium chloride, disodium phosphate, flavor, poloxamer 407, polysorbate 80, propylene plycol, red 33, sodium benzoate, sodium phosphate, sodium saccharin, sorbitol, water

Other information

- Store at room temperature

Distributed by: LEC Custom Products, Inc, Missisauga, ON L5S 1B8

MADE IN CANADA

PACKAGE LABEL

PERCARA™

ALCOHOL FREE

CAVITY PROTECTION

kids BUBBLE GUM

FLUORIDE RINSE

18 FL OZ (532 ML)